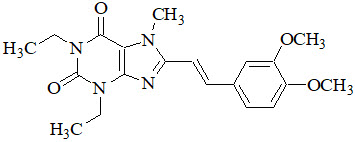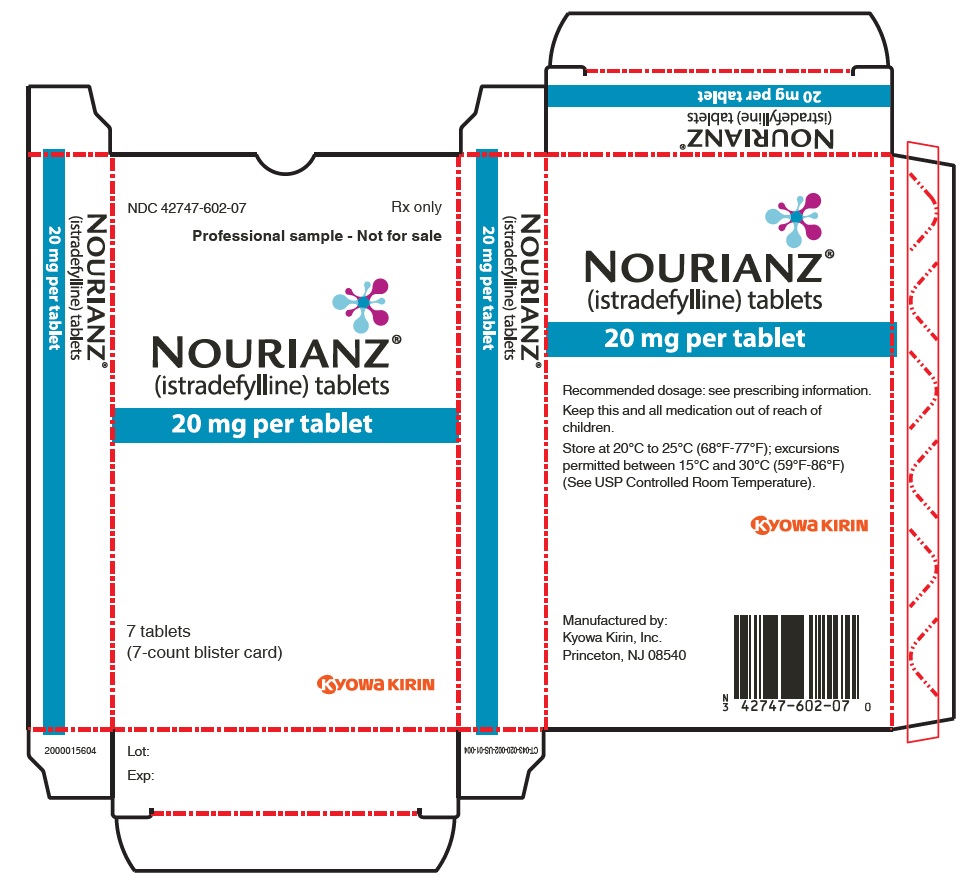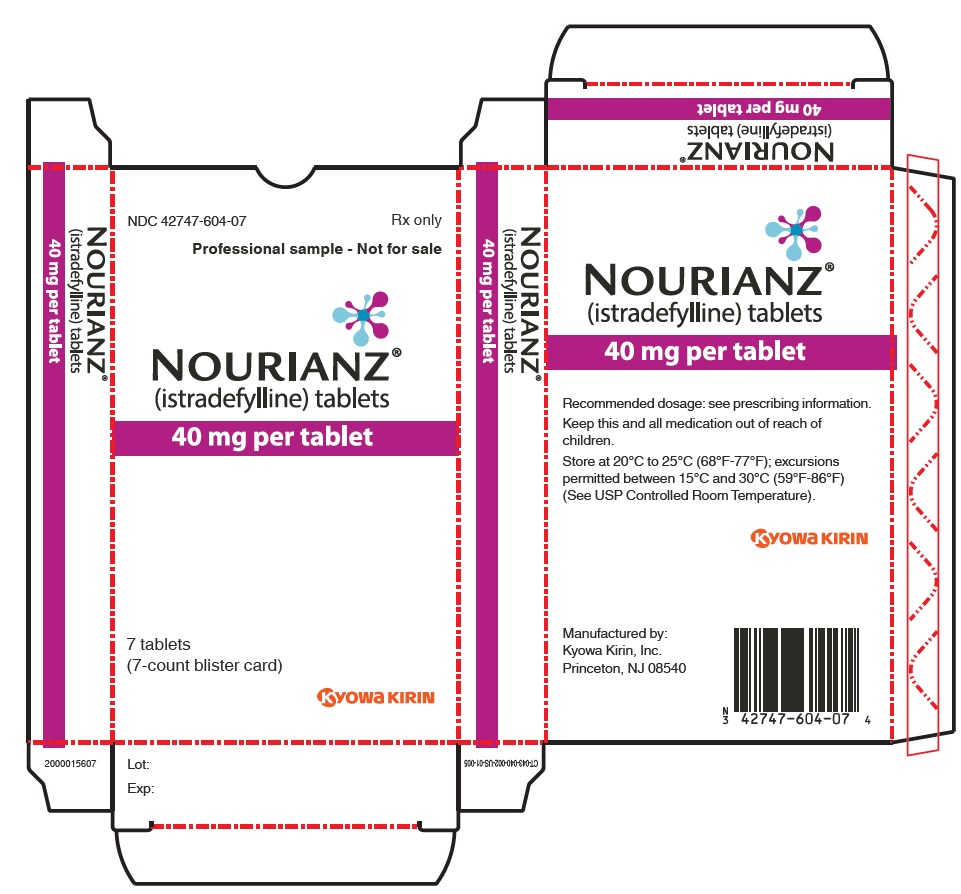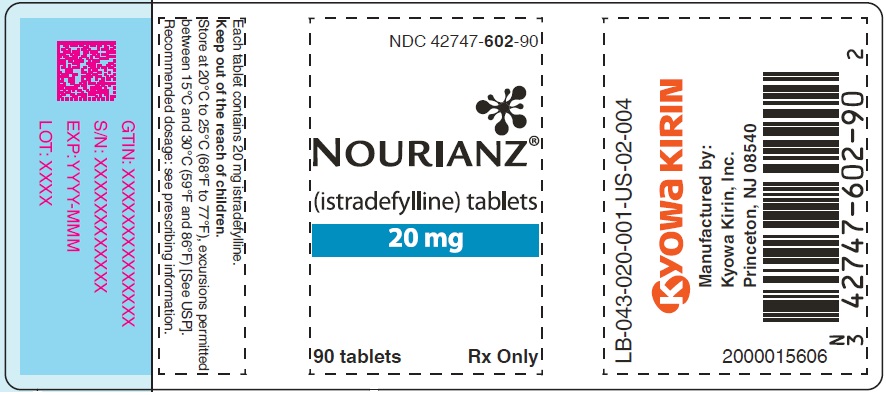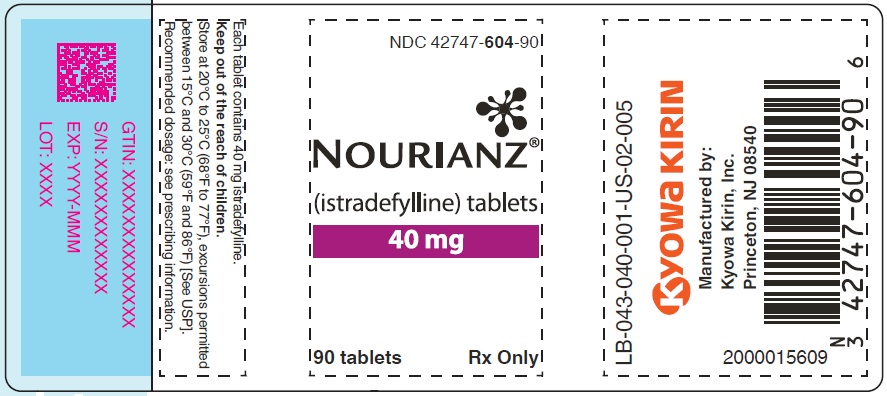 DRUG LABEL: NOURIANZ
NDC: 42747-602 | Form: TABLET, FILM COATED
Manufacturer: Kyowa Kirin, Inc.
Category: prescription | Type: HUMAN PRESCRIPTION DRUG LABEL
Date: 20250520

ACTIVE INGREDIENTS: istradefylline 20 mg/1 1
INACTIVE INGREDIENTS: Lactose Monohydrate; Microcrystalline Cellulose; CROSPOVIDONE; POLYVINYL ALCOHOL, UNSPECIFIED; Magnesium Stearate; Carnauba Wax

HIGHLIGHTS OF PRESCRIBING INFORMATION

These highlights do not include all the information needed to use NOURIANZ safely and effectively. See full prescribing information for NOURIANZ.
NOURIANZ® (istradefylline) tablets, for oral use
Initial U.S. Approval: 2019

1 INDICATIONS AND USAGE

NOURIANZ is an adenosine receptor antagonist indicated as adjunctive treatment to levodopa/carbidopa in adult patients with Parkinson's disease (PD) experiencing "off" episodes (1).

2 DOSAGE AND ADMINISTRATION

- The recommended dosage is 20 mg orally once daily. The dosage may be increased to a maximum of 40 mg once daily (2.1).
- May be taken with or without food (2.1).
- Patients with hepatic impairment: Maximum recommended dosage with moderate hepatic impairment is 20 mg once daily; use of NOURIANZ in patients with severe hepatic impairment should be avoided (2.4, 8.7).
- Patients who smoke 20 or more cigarettes per day (or the equivalent of another tobacco product): Recommended dosage is 40 mg once daily (2.5, 8.8).

3 DOSAGE FORMS AND STRENGTHS

Tablets: 20 mg and 40 mg (3).

4 CONTRAINDICATIONS

None (4).

5 WARNINGS AND PRECAUTIONS

- Dyskinesia: Monitor patients for dyskinesia or exacerbation of existing dyskinesia (5.1).
- Hallucinations / Psychotic Behavior: Consider dosage reduction or stopping NOURIANZ if occurs (5.2).
- Impulse Control / Compulsive Behaviors: Consider dosage reduction or stopping NOURIANZ if occurs (5.3).

6 ADVERSE REACTIONS

The most common adverse reactions (at least 5% and more frequent than placebo) were dyskinesia, dizziness, constipation, nausea, hallucination, and insomnia (6.1).

To report SUSPECTED ADVERSE REACTIONS, contact Kyowa Kirin Inc. at 1-844-768-3544 or FDA at 1-800-FDA-1088 or www.fda.gov/medwatch.

7 DRUG INTERACTIONS

- Strong CYP3A4 inhibitors: Recommended maximum dosage with concomitant use is 20 mg once daily (2.2, 7.1).
- Strong CYP3A4 inducers: Avoid use (2.3, 7.1).

8 USE IN SPECIFIC POPULATIONS

- Pregnancy: Based on animal data, may cause fetal harm (8.1).

FULL PRESCRIBING INFORMATION

1 INDICATIONS AND USAGE

NOURIANZ is indicated as adjunctive treatment to levodopa/carbidopa in adult patients with Parkinson's disease (PD) experiencing "off" episodes.

2 DOSAGE AND ADMINISTRATION

2.1 Dosing Information

The recommended dosage of NOURIANZ is 20 mg administered orally once daily. The dosage may be increased to a maximum of 40 mg once daily, based on individual need and tolerability. Initial dose titration is not required.

NOURIANZ can be taken with or without food [see Clinical Pharmacology (12.3)].

2.2 Dosage Adjustment with Strong CYP3A4 Inhibitors

The maximum recommended dosage of NOURIANZ with concomitant use of strong CYP3A4 inhibitors is 20 mg once daily [see Drug Interactions (7.1)].

2.3 Dosing with Strong CYP3A4 Inducers

Avoid use of NOURIANZ with strong CYP3A4 inducers [see Drug Interactions (7.1)].

2.4 Dosage Adjustment in Patients with Hepatic Impairment

The maximum recommended dosage of NOURIANZ in patients with moderate hepatic impairment (Child-Pugh Class B) is 20 mg once daily. Closely monitor patients with moderate hepatic impairment for adverse reactions when on NOURIANZ treatment [see Adverse Reactions (6.1)]. Avoid use of NOURIANZ in patients with severe hepatic impairment (Child-Pugh Class C) [see Use in Specific Populations (8.7)].

2.5 Dosage Adjustment for Tobacco Smokers

The recommended dosage of NOURIANZ in patients who use tobacco in amounts of 20 or more cigarettes per day (or the equivalent of another tobacco product) is 40 mg once daily [see Use in Specific Populations (8.8) and Clinical Pharmacology (12.3)].

3 DOSAGE FORMS AND STRENGTHS

- 20 mg tablets: Peach-colored, pillow-shaped, film-coated tablets with "20" debossed on one side.
- 40 mg tablets: Peach-colored, almond-shaped, film-coated tablets with "40" debossed on one side.

4 CONTRAINDICATIONS

None.

5 WARNINGS AND PRECAUTIONS

5.1 Dyskinesia

NOURIANZ in combination with levodopa may cause dyskinesia or exacerbate pre-existing dyskinesia.

In controlled clinical trials (Studies 1, 2, 3, and 4) [see Clinical Studies (14)], the incidence of dyskinesia was 15% for NOURIANZ 20 mg, 17% for NOURIANZ 40 mg, and 8% for placebo, in combination with levodopa. One percent of patients treated with either NOURIANZ 20 mg or 40 mg discontinued treatment because of dyskinesia, compared to 0% for placebo.

5.2 Hallucinations / Psychotic Behavior

Because of the potential risk of exacerbating psychosis, patients with a major psychotic disorder should not be treated with NOURIANZ. Consider dosage reduction or discontinuation if a patient develops hallucinations or psychotic behaviors while taking NOURIANZ.

In controlled clinical trials (Studies 1, 2, 3, and 4) [see Clinical Studies (14)], the incidence of hallucinations was 2% for NOURIANZ 20 mg, 6% for NOURIANZ 40 mg, and 3% for placebo. In patients treated with NOURIANZ 40 mg, 1% discontinued because of hallucinations, compared to 0% for placebo and 0% for patients treated with NOURIANZ 20 mg. The incidence of "abnormal thinking and behavior" (paranoid ideation, delusions, confusion, mania, disorientation, aggressive behavior, agitation, or delirium) reported as an adverse reaction was 1% for NOURIANZ 20 mg, 2% for NOURIANZ 40 mg, and 1% for placebo.

5.3 Impulse Control / Compulsive Behaviors

Patients treated with NOURIANZ and one or more medication(s) for the treatment of Parkinson's disease (including levodopa) may experience intense urges to gamble, increased sexual urges, intense urges to spend money, binge or compulsive eating, and/or other intense urges, and the inability to control these urges. In controlled clinical trials (Studies 1, 2, 3 and 4) [see Clinical Studies (14)], one patient treated with NOURIANZ 40 mg was reported to have impulse control disorder, compared to no patient on placebo or NOURIANZ 20 mg.

In some postmarketing cases, these urges were reported to have stopped when the dose was reduced, or the medication was discontinued. Because patients may not recognize these behaviors as abnormal, it is important for prescribers to specifically ask patients or their caregivers about the development of new or increased gambling urges, sexual urges, uncontrolled spending, binge or compulsive eating, or other urges while being treated with NOURIANZ. Consider dose reduction or discontinuation if a patient develops such urges while taking NOURIANZ [see Adverse Reactions (6.2)].

6 ADVERSE REACTIONS

The following clinically significant adverse reactions are discussed in greater detail in other sections of the labeling:

- Dyskinesia [see Warnings and Precautions (5.1)]
- Hallucinations / Psychotic Behavior [see Warnings and Precautions (5.2)]
- Impulse Control / Compulsive Behaviors [see Warnings and Precautions (5.3)]

6.1 Clinical Trials Experience

Because clinical trials are conducted under widely varying conditions, adverse reaction rates observed in the clinical trials of a drug cannot be directly compared to rates in the clinical trials of another drug and may not reflect the rates observed in practice.

The safety of NOURIANZ was evaluated in 734 patients with Parkinson's disease (PD) taking a stable dose of levodopa and a DOPA decarboxylase inhibitor, with or without other PD medications, in four randomized, multicenter, double-blind, placebo-controlled trials 12 weeks in duration (Studies 1, 2, 3 and 4) [see Clinical Studies (14)]. Of the patient population exposed to NOURIANZ, 50% were male, 32% White, 67% Asian, and the mean age was 65 years (range: 33 to 84 years). Of these patients, 356 received NOURIANZ 20 mg and 378 received NOURIANZ 40 mg.

Adverse Reactions Leading to Discontinuation of Treatment

The incidence of patients discontinuing for any adverse reaction was 5% for NOURIANZ 20 mg, 6% for NOURIANZ 40 mg, and 5% for placebo. The most frequently reported adverse reaction causing study discontinuation was dyskinesia [see Warnings and Precautions (5.1)].

Common Adverse Reactions in Pooled Placebo-Controlled Trials

Table 1 shows adverse reactions with a frequency of at least 2% in patients treated with NOURIANZ 20 mg or 40 mg once daily. The most common adverse reactions in which the frequency for NOURIANZ was at least 5%, and greater than the incidence on placebo, were dyskinesia, dizziness, constipation, nausea, hallucination, and insomnia.

Table 1: Adverse Reactions with an Incidence of at Least 2% in Patients Treated with NOURIANZ, and Greater than on Placebo, in Pooled Studies 1, 2, 3, and 4
Adverse Reactions | NOURIANZ 20 mg/day (N=356) % | NOURIANZ 40 mg/day (N=378) % | Placebo N=426 (%)
Nervous system disorders
Dyskinesia | 15 | 17 | 8
Dizziness | 3 | 6 | 4
Gastrointestinal disorders
Constipation | 5 | 6 | 3
Nausea | 4 | 6 | 5
Diarrhea | 1 | 2 | 1
Psychiatric disorders
Hallucination [Includes hallucinations, hallucinations visual, hallucinations olfactory, hallucinations somatic, hallucinations auditory.] | 2 | 6 | 3
Insomnia | 1 | 6 | 4
Metabolism and nutrition disorders
Decreased appetite | 1 | 3 | 1
Investigations
Blood alkaline phosphatase increased | 1 | 2 | 1
Blood glucose increased | 1 | 2 | 0
Blood urea increased | 1 | 2 | 0
Respiratory, thoracic and mediastinal disorders
Upper Respiratory Tract Inflammation | 1 | 2 | 0
Skin and subcutaneous tissue disorders
Rash | 1 | 2 | 1

6.2 Postmarketing Experience

The following adverse reaction has been identified during post approval use of istradefylline outside of the United States. Because these reactions are reported voluntarily from a population of uncertain size, it is not always possible to reliably estimate their frequency or establish a causal relationship to drug exposure: increased libido.

7 DRUG INTERACTIONS

7.1 Effect of Other Drugs on NOURIANZ

Strong CYP3A4 Inhibitors

Coadministration of NOURIANZ with a strong CYP3A4 inhibitor (ketoconazole) increased istradefylline AUCinf by 2.5-fold [see Clinical Pharmacology (12.3)]. Therefore, the recommended maximum dosage of NOURIANZ in patients concomitantly using strong CYP3A4 inhibitors (e.g., itraconazole, ketoconazole, clarithromycin) is 20 mg once daily [see Dosage and Administration (2.2)].

Strong CYP3A4 Inducers

Coadministration of NOURIANZ with a strong CYP3A4 inducer (rifampin) decreased istradefylline Cmax and AUCinf by 45% and 81%, respectively [see Clinical Pharmacology (12.3)]. Therefore, it is recommended to avoid use of NOURIANZ with strong CYP3A4 inducers (e.g., carbamazepine, rifampin, phenytoin, St. John's wort) [see Dosage and Administration (2.3)].

7.2 Effect of NOURIANZ on Other Drugs

CYP3A4 Substrates

Coadministration of NOURIANZ 20 mg with a CYP3A4 substrate (midazolam) did not affect the CYP3A4 substrate exposure, while concomitant administration of NOURIANZ 40 mg increased the CYP3A4 substrate (atorvastatin) Cmax and AUCinf by 1.5-fold [see Clinical Pharmacology (12.3)]. Monitor for an increase in adverse reactions of concomitant drugs that are CYP3A4 substrates when coadministering with NOURIANZ 40 mg.

P-glycoprotein (P-gp) Substrates

Coadministration of NOURIANZ with a P-gp substrate (digoxin) increased the P-gp substrate Cmax and AUCinf by 33% and 21%, respectively [see Clinical Pharmacology (12.3)]. Monitor for an increase in adverse reactions of concomitant drugs that are P-gp substrates when coadministering with NOURIANZ.

8 USE IN SPECIFIC POPULATIONS

8.1 Pregnancy

Risk Summary

There are no adequate data on the developmental risk associated with the use of NOURIANZ in pregnant women. In animal studies (see Data), oral administration of istradefylline during pregnancy resulted in teratogenicity (increased incidences of fetal structural abnormalities, embryofetal and offspring mortality and growth deficits) at clinically relevant exposures and in the absence of maternal toxicity. The teratogenic effects of istradefylline in pregnant rabbits were substantially greater when administered in combination with levodopa/carbidopa than when administered alone.

The estimated background risk of major birth defects and miscarriage for the indicated population is unknown. In the U.S. general population, the estimated background risks of major birth defects and miscarriage in clinically recognized pregnancies are 2-4% and 15-20%, respectively.

Data

Animal Data

Oral administration of istradefylline (0, 40, 200, or 1000 mg/kg/day) to pregnant rats throughout organogenesis resulted in decreased fetal body weight and increased fetal skeletal and visceral variations at the highest dose tested. Plasma exposure (AUC) at the no-effect dose for adverse effects on embryofetal development in rats (200 mg/kg/day) is approximately 4 times that in humans at the maximum recommended human dose (MRHD) of 40 mg.

Oral administration of istradefylline (0, 50, 200, or 800 mg/kg/day) to pregnant rabbits throughout organogenesis resulted in increased embryofetal mortality at the mid and high doses, increased fetal malformations (external, visceral, skeletal) at all doses, and reduced fetal body weight at the highest dose tested. A no-effect dose for adverse effects on embryofetal development in rabbits was not identified. Plasma exposure (AUC) at the lowest dose tested (50 mg/kg/day) is less than that in humans at the MRHD.

In pregnant rabbits, oral administration of istradefylline (0, 50, 200, or 400 mg/kg/day) alone or in combination with oral levodopa/carbidopa (80/20 mg/kg/day) throughout the period of organogenesis resulted in an increase in embryofetal mortality and an increase (marked at the high dose) in malformations (including limb reduction, craniofacial, and cardiovascular) in fetuses from rats administered istradefylline at all doses in combination with levodopa/carbidopa. Istradefylline alone resulted in an increase in embryofetal mortality and visceral malformations; no increase in fetal malformations was observed with levodopa/carbidopa alone. Fetal body weight was reduced by istradefylline alone (400 mg/kg/day) and in combination (200 and 400 mg/kg/day) with levodopa/carbidopa. A no-effect dose for adverse effects on embryofetal development in rabbits when istradefylline was administered in combination with levodopa/carbidopa was not identified. Plasma exposure (AUC) at the lowest dose of istradefylline tested (50 mg/kg/day) in combination with levodopa/carbidopa is less than that in humans at the MRHD.

Oral administration of istradefylline (0, 6, 25, 100, or 400 mg/kg/day) to female rats throughout gestation and lactation resulted in decreased pup survival and reduced pup body weight (which persisted into adulthood) at all but the lowest dose tested. Exposure to drug in the milk may have contributed to these effects, as demonstrated in pups of untreated (control) dams reared by dams receiving istradefylline (400 mg/kg/day). No adverse effects were observed on physical or neurobehavioral development, or reproductive function. Plasma exposure at the no-effect dose for adverse effects on pre- and postnatal development in rats (6 mg/kg/day) is less than that in humans at the MRHD.

8.2 Lactation

Risk Summary

There are no data on the presence of istradefylline in human milk, the effects of istradefylline on the breastfed infant, or the effects of istradefylline on milk production. Istradefylline was present in the milk of lactating rats at concentrations up to 10 times that in maternal plasma.

The developmental and health benefits of breastfeeding should be considered along with the mother's clinical need for NOURIANZ, and any potential adverse effects on the breastfed infant from NOURIANZ or from the underlying maternal condition.

8.3 Females and Males of Reproductive Potential

Contraception

Use of NOURIANZ during pregnancy is not recommended. Women of childbearing potential should be advised to use contraception during treatment with NOURIANZ [see Use in Specific Populations (8.1)].

8.4 Pediatric Use

Safety and effectiveness in pediatric patients have not been established.

8.5 Geriatric Use

No adjustment of NOURIANZ dosage is recommended on the basis of age. Of the total number of PD patients who received NOURIANZ in clinical trials, 53% were ≥65 years and 13% were ≥75 years of age. No overall differences in effectiveness were observed between these patients and younger patients.

8.6 Renal Impairment

No adjustment of NOURIANZ dosage is needed in patients with mild renal impairment (estimated creatinine clearance (CrCL) by Cockcroft-Gault equation: 60-89 mL/min), moderate renal impairment (CrCL 30-59 mL/min), or severe renal impairment (CrCL 15-29 mL/min). NOURIANZ has not been evaluated in patients with end-stage renal disease (ESRD) (CrCL <15 mL/min) or ESRD requiring hemodialysis [see Clinical Pharmacology (12.3)].

8.7 Hepatic Impairment

No adjustment of NOURIANZ dosage is needed in patients with mild hepatic impairment (Child-Pugh Class A).

In patients with moderate hepatic impairment (Child-Pugh Class B), the steady-state exposures (AUC0-24h) were predicted to be 3.3-fold higher than in healthy subjects, based on the estimated mean terminal half-life. Therefore, the maximum recommended dosage of NOURIANZ in patients with moderate hepatic impairment (Child-Pugh Class B) is 20 mg once daily [see Clinical Pharmacology (12.3)]. Closely monitor patients with moderate hepatic impairment for adverse events when on NOURIANZ treatment [see Adverse Reactions (6.1)].

NOURIANZ has not been studied in patients with severe hepatic impairment (Child-Pugh Class C). Avoid use of NOURIANZ in patients with severe hepatic impairment [see Clinical Pharmacology (12.3)].

8.8 Tobacco Smokers

Tobacco smoking decreased NOURIANZ steady-state systemic exposures by 38% to 54% [see Clinical Pharmacology (12.3)], which may decrease efficacy. Therefore, the recommended NOURIANZ dosage in patients who smoke 20 or more cigarettes per day (or the equivalent amount of another tobacco product) is 40 mg once daily.

10 OVERDOSAGE

10.1 Human Experience

There is limited clinical experience regarding human overdosage with NOURIANZ. In clinical trials, one patient took 6 tablets (120 mg, 3 times the maximum recommended dosage) of istradefylline with alcoholic beverages and developed hallucinations, agitation, and worsening dyskinesia.

10.2 Management of Overdose

There are no known specific antidotes for NOURIANZ nor any specific treatment for istradefylline overdose. If an overdose occurs, NOURIANZ treatment should be discontinued and supportive treatment should be administered as clinically indicated. Consider the long terminal half-life of istradefylline (about 83 hours) and the possibility of multiple drug involvement.

Consult a Certified Poison Control Center for up-to-date guidance and advice.

11 DESCRIPTION

NOURIANZ contains istradefylline, an adenosine receptor antagonist, which has a xanthine derivative structure. The chemical name is (E)-8-(3,4-dimethoxystyryl)-1,3-diethyl-7-methyl-3,7-dihydro-1H-purine-2,6-dione. Its molecular formula is C20H24N4O4. The molecular weight is 384.43. Istradefylline has the following structural formula:

Istradefylline is a light yellow-green crystalline powder. Istradefylline has a dissociation constant (pKa) of 0.78. The aqueous solubility of istradefylline is ~0.5 µg/mL across the physiological pH range and 0.6 µg/mL in water.

NOURIANZ tablets are intended for oral administration only. Each tablet contains 20 mg or 40 mg of istradefylline and the following inactive ingredients: crospovidone, lactose monohydrate, magnesium stearate, microcrystalline cellulose, and polyvinyl alcohol. The film coating contains hypromellose, lactose monohydrate, polyethylene glycol 3350, titanium dioxide, triacetin, and the following dyes: iron oxide red and iron oxide yellow. Carnauba wax is used for polishing.

12 CLINICAL PHARMACOLOGY

12.1 Mechanism of Action

The precise mechanism by which istradefylline exerts its therapeutic effect in Parkinson’s disease is unknown. In in vitro studies and in in vivo animal studies, istradefylline was demonstrated to be an adenosine A2A receptor antagonist.

12.2 Pharmacodynamics

Cardiac Electrophysiology

The effect of NOURIANZ (40 mg or 160 mg [4 times the maximum recommended dosage] once daily for 14 days) on the QTc interval was evaluated in a randomized, placebo and moxifloxacin-controlled, multiple-dose, blinded, parallel group study. There was no clinically significant prolongation of QTc interval or relationship between changes in QTc and concentrations of istradefylline.

12.3 Pharmacokinetics

Istradefylline exhibits dose-proportional pharmacokinetics after multiple oral doses from 20 mg to 80 mg (2 times the maximum recommended dosage). Steady-state was reached within 2 weeks of once-daily dosing. The pharmacokinetics of istradefylline were similar in PD patients and healthy subjects.

Absorption

The median time to reach the maximum concentration (Tmax) for istradefylline was about 4 hours under fasted dosing conditions.

Effect of Food

Istradefylline exposure, represented by the area under the curve over time to infinity (AUCinf), increased 1.25-fold when NOURIANZ was coadministered with a standard high-fat meal, compared with administration in a fasted state. Istradefylline maximum plasma concentrations (Cmax) increased by 1.64-fold and Tmax was shortened by 1 hour when NOURIANZ was administered with a high-fat meal. These differences in pharmacokinetic parameters are not expected to be clinically significant [see Dosage and Administration (2.1)].

Distribution

The plasma protein binding of istradefylline was approximately 98%. The apparent volume of distribution (Vd/F) of istradefylline is approximately 557 liters.

Elimination

The total clearance of istradefylline is approximately 4.6 L/hour. The mean terminal half-life (t1/2) for istradefylline at steady-state is approximately 83 hours.

Metabolism

In humans, istradefylline is exclusively eliminated via metabolism. In vitro studies indicate that istradefylline is primarily metabolized via CYP1A1 and CYP3A4, with minor contribution from CYP1A2, 2B6, 2C8, CYP2C9, CYP2C18, and 2D6. Six metabolites have been identified in human plasma. These metabolites each account for less than 10% of the exposure of the parent drug.

Excretion

Approximately 48% of a 40-mg oral dose of ^14C-istradefylline was eliminated in feces, and 39% in urine. Unchanged istradefylline was not detected in urine.

Specific Populations

In patients with moderate hepatic impairment (Child-Pugh Class B), the steady-state exposure (AUC0-24) of istradefylline is predicted to be 3.3-fold higher relative to healthy subjects, based on the estimated mean terminal half-life [see Use in Specific Populations (8.7)]. Based on population pharmacokinetic analyses, no clinically relevant changes in the pharmacokinetics of istradefylline were observed based on age, sex, weight, or race. No clinically relevant changes in istradefylline exposure were observed in patients with severe renal impairment (CrCL 15-29 mL/min) or mild hepatic impairment. NOURIANZ has not been studied in patients with ESRD (CrCL < 15 mL/min), ESRD patients requiring hemodialysis, or severe hepatic impairment (Child-Pugh Class C) [see Use in Specific Populations (8.6, 8.7)].

Steady-state systemic exposure to istradefylline (40 mg) is 38% to 54% lower in tobacco smokers (who smoke 20 or more cigarettes per day) when compared with non-smokers matched for age, gender, and body weight [see Specific Populations (8.8)].

Drug Interaction Studies

In Vitro Assessment of Drug Interactions

Drug-Metabolizing Enzyme Inhibition

Istradefylline is a weak inhibitor of CYP3A4, but not an inhibitor of CYP1A2, 2B6, 2C9, 2C19, or 2D6 in vitro.

Drug-Metabolizing Enzyme Induction

Istradefylline was a weak inducer of CYP3A4 but not an inducer of CYP1A2 and 2B6 when tested in vitro. However, clinical drug-drug interaction studies with a CYP3A4 substrate (i.e., midazolam) showed no induction of CYP3A4.

Transporters

Istradefylline was not a substrate for drug transporters P-gp, BCRP, OATP1B1, or OATP1B3 when tested in vitro. Istradefylline was a weak inhibitor for P-gp, BCRP, OATP1B1, OATP1B3, OAT1, OCT2, MATE1, and MATE2-K, but not an inhibitor of OAT3 when tested in vitro.

In Vivo Assessment of Drug Interactions

Effect of Other Drugs on Istradefylline

Strong CYP3A4 Inhibitors

Coadministration of ketoconazole (200 mg twice daily for 4 days) with a single dose of istradefylline (40 mg) increased the AUCinf of istradefylline by 2.5-fold, but had no effect on Cmax [see Drug Interactions (7.1)].

Strong CYP3A4 Inducers

Coadministration of rifampin (600 mg daily for 20 days) with a single dose of istradefylline (40 mg) reduced the Cmax and AUCinf of istradefylline by 45% and 81% respectively, when compared with istradefylline administered alone [see Drug Interactions (7.1)].

Effect of Istradefylline on Other Drugs

CYP3A4 Substrates

Coadministration of istradefylline at higher than the recommended doses (80 mg for 14 days) with a single dose of midazolam (10 mg) increased midazolam AUCinf 2.4-fold, and Cmax by 1.6-fold, when compared with midazolam administered alone. Coadministration of lower doses of istradefylline (5 mg and 20 mg) with midazolam (7.5 mg) did not have these effects [see Drug Interactions (7.2)].

Coadministration of istradefylline (40 mg daily for 17 days) with a single dose of atorvastatin (40 mg) increased the Cmax and AUCinf of atorvastatin by 1.5-fold, compared with atorvastatin alone [see Drug Interactions (7.2)].

P-glycoprotein Substrates

Coadministration of istradefylline (40 mg daily for 21 days) with a single dose of digoxin (0.4 mg) increased the Cmax and AUCinf of digoxin by 33% and 21%, respectively, when compared with digoxin alone [see Drug Interactions (7.2)].

Carbidopa/Levodopa

Coadministration of istradefylline (80 mg [two times the recommended maximum dosage] daily for 14 days) with a single dose of carbidopa/levodopa (50/200 mg) did not affect the pharmacokinetics of carbidopa/levodopa. Also, coadministration of istradefylline (20 mg or 40 mg daily for 14 days) with carbidopa/levodopa (25/100 mg three times a day for 14 days) did not affect the systemic exposure of carbidopa/levodopa.

13 NONCLINICAL TOXICOLOGY

13.1 Carcinogenesis, Mutagenesis, and Impairment of Fertility

Carcinogenesis

In lifetime oral carcinogenicity studies, there was no evidence of carcinogenicity in mouse (0, 25, 125, or 250 mg/kg) or rat (0, 30, 100, or 320 mg/kg). Plasma exposures (AUC) at the highest doses tested were approximately 20 (mouse) and 10 (rat) times that in humans at the maximum recommended human dose (MRHD) of 40 mg/day.

Mutagenesis

Istradefylline was negative in in vitro (bacterial reverse mutation assay, chromosomal aberration in mammalian cells) and in vivo (mouse bone marrow micronucleus) assays.

Impairment of Fertility

Oral administration of istradefylline (0, 160, 360, or 800 mg/kg/day) to male and female rats prior to and during mating and continuing in females to gestation day 7 resulted in a decrease in fertility at the highest dose tested and an increase in preimplantation loss at the mid and high doses. Sperm motility was reduced at the highest dose tested. Plasma exposure (AUC) at the no-effect dose (160 mg/kg) for adverse effects on reproductive function is approximately 3 times that in humans at the MRHD.

13.2 Animal Toxicology and/or Pharmacology

Oral administration of istradefylline (0, 30, 100, or 320 mg/kg/day) to rats for two years resulted in an increase in the incidence and severity of vascular mineralization in the brain (including in the caudate/putamen, globus pallidus, thalamus, and nucleus accumbens) at all doses tested. The vascular mineralization was composed of calcium and phosphorus and, at higher doses, were reported to partially or completely occlude the blood vessels. There was no evidence of neuronal degeneration, inflammation, or glial response associated with the foci of mineralization.

Brain mineralization was not detected in mice administered istradefylline (0, 25, 125, or 250 mg/kg/day) orally for two years or in dogs administered istradefylline (0, 10, 30, or 100 mg/kg/day) orally for 52 weeks.

14 CLINICAL STUDIES

The efficacy of NOURIANZ for the adjunctive treatment to levodopa/carbidopa in patients with Parkinson's disease experiencing "off" episodes was shown in four randomized, multicenter, double-blind, 12-week, placebo-controlled studies (Study 1, NCT00456586; Study 2, NCT00199407; Study 3, NCT00455507; and Study 4, NCT00955526). The studies enrolled patients with a mean duration of Parkinson's disease of 9 years (range: 1 month to 37 years) that were Hoehn and Yahr Stage II to IV, experiencing at least 2 hours (mean approximately 6 hours) of "off" time per day, and were treated with levodopa for at least one year, with stable dosage for at least 4 weeks before screening (mean total daily dosage range: 416 to 785 mg). Patients continued levodopa treatment with or without concomitant PD medications, including dopamine agonists (85%), COMT inhibitors (38%), MAO-B inhibitors (40%), anticholinergics (13%), and/or amantadine (33%), provided the medications were stable for at least 4 weeks before screening and throughout the study period. The studies excluded patients who had received a neurosurgical treatment for PD (e.g., pallidotomy, thalamotomy, deep brain stimulation).

The primary efficacy endpoint was the change from baseline in the daily awake percentage of "off" time, or the change from baseline in total daily "off" time, based on 24-hour diaries completed by patients. A change from baseline in "on" time without troublesome dyskinesia (i.e., "on" time without dyskinesia plus "on" time with non-troublesome dyskinesia) was a secondary efficacy endpoint.

Study 1 was conducted in the U.S. and Canada, and Study 2 was conducted in the U.S. In these studies, patients were randomized to once-daily treatment with NOURIANZ 20 mg, 40 mg, or placebo. Patients treated with NOURIANZ 20 mg or NOURIANZ 40 mg once daily experienced a statistically significant decrease from baseline in percentage of daily awake "off" time, compared with patients on placebo, as summarized in Table 2.

Table 2: Studies 1 and 2: Change From Baseline in Daily Awake OFF Time
 | Baseline |  | Change from Baseline to Endpoint
 | N | (mean ± SD) % of awake "off" hours | N | (LSMD [LSMD: Least squares mean difference; a negative value indicates a greater reduction from baseline in Percentage Daily Awake "off" time for NOURIANZ, relative to placebo.] vs. placebo), % awake "off" hours, (p-value)
Study 1
Placebo | 66 | 37.2 ± 13.8 | 65 | --
NOURIANZ 40 mg | 129 | 38.4 ± 16.2 | 126 | - 6.78 (p=0.007)
Study 2
Placebo | 113 | 38.7 ± 11.6 | 113 | --
NOURIANZ 20 mg | 112 | 39.8 ± 14.0 | 112 | - 4.57 (p=0.025)
SD: Standard Deviation

Compared with patients on placebo, patients treated with NOURIANZ experienced an additional increase from baseline in "on" time without troublesome dyskinesia of 0.96 hours (nominal p=0.026) in Study 1, and of 0.55 hours (nominal p=0.135) in Study 2.

Study 3 and Study 4 were conducted in Japan. In these studies, patients were randomized equally to treatment with NOURIANZ 20 mg, 40 mg, or placebo. Patients treated with NOURIANZ 20 mg or NOURIANZ 40 mg once daily experienced a statistically significant decrease from baseline in "off" time compared with patients on placebo, as summarized in Table 3.

Table 3: Studies 3 and 4: Change From Baseline in Daily OFF Time
 | Baseline |  | Change from Baseline to Endpoint
 | N | (mean ± SD) hours | N | (LSMD [LSMD: Least squares mean difference; a negative value indicates a greater reduction from baseline in "off" time for NOURIANZ, relative to placebo.] vs. placebo) hours (p-value)
Study 3
Placebo | 118 | 6.4 ± 2.7 | 118 | --
NOURIANZ 20 mg | 115 | 6.8 ± 2.9 | 115 | -0.65 (p=0.028)
NOURIANZ 40 mg | 124 | 6.6 ± 2.5 | 124 | -0.92 (p=0.002)
Study 4
Placebo | 123 | 6.3 ± 2.5 | 123 | --
NOURIANZ 20 mg | 120 | 6.6 ± 2.7 | 120 | -0.76 (p=0.006)
NOURIANZ 40 mg | 123 | 6.0 ± 2.5 | 123 | -0.74 (p=0.008)
SD: Standard Deviation

In Study 3, compared with placebo, an additional increase from baseline in "on" time without troublesome dyskinesia of 0.57 hours (nominal p=0.085) and of 0.65 hours (nominal p=0.048), respectively, were observed in patients treated with NOURIANZ 20 mg or NOURIANZ 40 mg. In Study 4, the corresponding increases in "on" time without troublesome dyskinesia were 0.83 hours (nominal p=0.008) for NOURIANZ 20 mg and 0.81 hours (nominal p=0.008) for NOURIANZ 40 mg.

16 HOW SUPPLIED/STORAGE AND HANDLING

16.1 How Supplied

NOURIANZ (istradefylline) tablets are available as:

20 mg Tablets:

Peach-colored, pillow-shaped, film-coated tablets with "20" debossed on one side.

Bottle of 90: NDC 42747-602-90

40 mg Tablets:

Peach-colored, almond-shaped, film-coated tablets with "40" debossed on one side.

Bottle of 90: NDC 42747-604-90

16.2 Storage and Handling

Store at 20°C to 25°C (68°F to 77°F); excursions permitted between 15°C and 30°C (59°F to 86°F) [see USP Controlled Room Temperature].

17 PATIENT COUNSELING INFORMATION

Advise the patient to read the FDA-approved patient labeling (Patient Information).

Dyskinesia

Advise patients that NOURIANZ may cause dyskinesia or exacerbate pre-existing dyskinesia [see Warnings and Precautions (5.1)].

Hallucinations / Psychotic Behavior

Advise patients that NOURIANZ may cause hallucinations or psychotic behavior and they should report any of these adverse reactions to their healthcare provider [see Warnings and Precautions (5.2)].

Impulse Control / Compulsive Behaviors

Inform patients that they may experience intense urges to gamble, increased sexual urges, and other intense urges and the inability to control these urges while taking NOURIANZ and one or more medication(s) for the treatment of Parkinson's disease (including levodopa). Advise patients that they should report any of these adverse reactions to their healthcare provider [see Warnings and Precautions (5.3)].

Concomitant Medications

Certain medications can cause an interaction with NOURIANZ. Advise patients to inform their healthcare provider about their smoking status and about all of the medicines they are taking or plan to take, including over-the-counter medicines, dietary supplements, and herbal products [see Drug Interactions (7.1, 7.2) and Use in Specific Populations (8.8)].

NOURIANZ® (istradefylline)
Manufactured by:
Kyowa Kirin, Inc.
Princeton, NJ 08540

Patient Information
NOURIANZ® (nue'–ree–anz)
(istradefylline)
tablets, for oral use

What is NOURIANZ?
NOURIANZ is a prescription medicine used with levodopa and carbidopa to treat adults with Parkinson's disease (PD) who are having "off" episodes.
It is not known if NOURIANZ is safe and effective in children.

Before you take NOURIANZ, tell your healthcare provider about all your medical conditions, including if you:

- have a history of abnormal movement (dyskinesia).
- have reduced liver function.
- smoke cigarettes.
- are pregnant or plan to become pregnant. NOURIANZ may harm your unborn baby.
- are breastfeeding or plan to breastfeed. It is not known if NOURIANZ passes into breast milk. You and your healthcare provider should decide if you will take NOURIANZ or breastfeed.

Tell your healthcare provider about all the medicines you take, including prescription and over-the-counter medicines, vitamins, and herbal supplements.
NOURIANZ and other medicines may affect each other causing side effects. NOURIANZ may affect the way other medicines work, and other medicines may affect how NOURIANZ works.
Know the medicines you take. Keep a list of them to show your healthcare provider and pharmacist when you get a new medicine.

How should I take NOURIANZ?

- Take NOURIANZ exactly as your healthcare provider tells you to.
- Take NOURIANZ one time each day.
- You can take NOURIANZ with or without food.
- If you take too much NOURIANZ, call your health care provider or go to the nearest hospital emergency room right away.

What are the possible side effects of NOURIANZ?
NOURIANZ may cause serious side effects, including:

- uncontrolled sudden movements (dyskinesia). Uncontrolled sudden movements is one of the most common side effects. NOURIANZ may cause uncontrolled sudden movements or make such movements you already have worse or more frequent. Tell your healthcare provider if this happens.
- hallucinations and other symptoms of psychosis. NOURIANZ can cause abnormal thinking and behavior including:

- being overly suspicious or feeling people want to harm you (paranoid ideation)
- believing things that are not real (delusions)
- seeing or hearing things that are not real (hallucinations)
- confusion
- increase activity or talking (mania)

- disorientation
- aggressive behavior
- agitation
- delirium (decreased awareness of things around you)

If you have hallucinations or any other abnormal thinking or behavior, talk with your healthcare provider.

- unusual urges (impulse control or compulsive behaviors). Some people taking NOURIANZ get urges to behave in a way unusual for them. Examples of this are unusual urges to gamble, increased sexual urges, strong urges to spend money, binge eating, and the inability to control these urges. If you notice or your family notices that you are developing any unusual behaviors, talk to your healthcare provider.

The most common side effects of NOURIANZ include uncontrolled movements (dyskinesia), dizziness, constipation, nausea, hallucinations, and problems sleeping (insomnia).
These are not all the possible side effects of NOURIANZ.
Call your doctor for medical advice about side effects. You may report side effects to FDA at 1-800-FDA-1088.

How should I store NOURIANZ?

- Store NOURIANZ at room temperature between 68°F to 77°F (20°C to 25°C).
- Keep NOURIANZ and all medicines out of the reach of children.

General information about the safe and effective use of NOURIANZ.
Medicines are sometimes prescribed for purposes other than those listed in a Patient Information leaflet. Do not use NOURIANZ for a condition for which it was not prescribed. Do not give NOURIANZ to other people, even if they have the same symptoms that you have. It may harm them. You can ask your healthcare provider or pharmacist for information about NOURIANZ that is written for health professionals.

What are the ingredients in NOURIANZ?
Active ingredient: istradefylline
Inactive ingredients: crospovidone, lactose monohydrate, magnesium stearate, microcrystalline cellulose, polyvinyl alcohol, hypromellose, polyethylene glycol 3350, titanium dioxide, triacetin, iron oxide red, iron oxide yellow, and carnauba wax.
Manufactured by: Kyowa Kirin, Inc., Princeton, NJ 08540 U.S.
NOURIANZ is a registered trademark of Kyowa Kirin, Inc.
For more information, call 1-844-768-3544 or go to www.NOURIANZ.com.

This Patient Information has been approved by the U.S. Food and Drug Administration

Issued: 3/2023

PRINCIPAL DISPLAY PANEL - 20 mg Tablet Label

NDC 42747-602-90

NOURIANZ®
(istradefylline) tablets

20 mg

90 tablets
Rx Only
KYOWA KIRIN

PRINCIPAL DISPLAY PANEL - 20 mg Tablet Carton Label

NDC 42747-602-07
Rx Only

NOURIANZ®
(istradefylline) tablets

20 mg per tablet

7 tablets
(7-count blister card)
KYOWA KIRIN

PRINCIPAL DISPLAY PANEL - 40 mg Tablet Label

NDC 42747-604-90

NOURIANZ®
(istradefylline) tablets

40 mg

90 tablets
Rx Only
KYOWA KIRIN

PRINCIPAL DISPLAY PANEL - 40 mg Tablet Carton Label

NDC 42747-604-07
Rx Only

NOURIANZ®
(istradefylline) tablets

40 mg per tablet

7 tablets
(7-count blister card)
KYOWA KIRIN